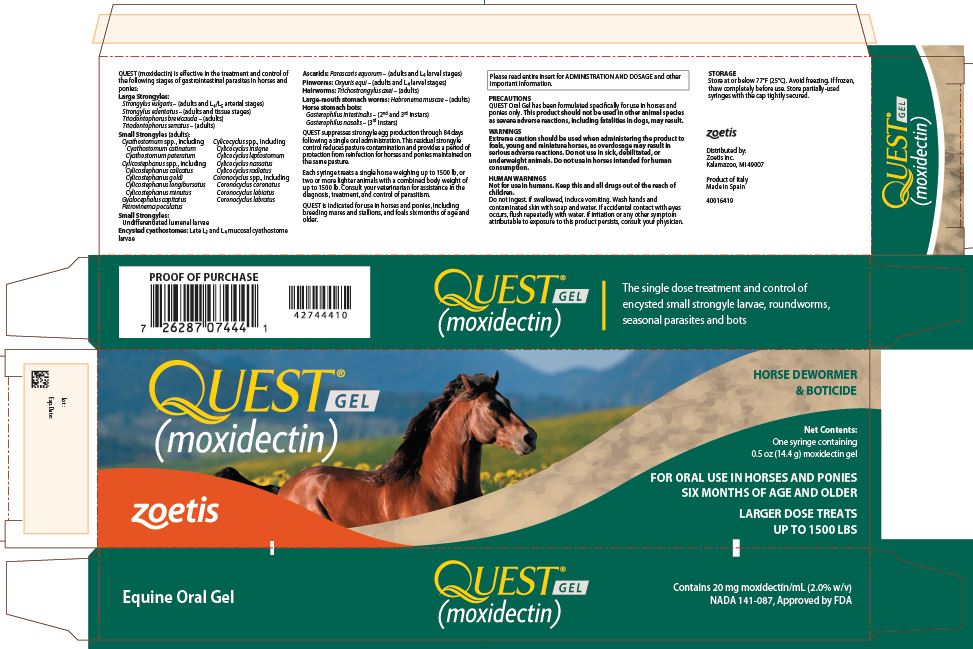 DRUG LABEL: Quest
NDC: 54771-7441 | Form: GEL
Manufacturer: Zoetis Inc.
Category: animal | Type: OTC ANIMAL DRUG LABEL
Date: 20180131

ACTIVE INGREDIENTS: MOXIDECTIN 19.5 mg/1 g

QUEST® GEL
(moxidectin)

2% Equine Oral Gel

Contains 20 mg moxidectin/mL
(2.0% w/v)

DEWORMER & BOTICIDE

FOR ORAL USE IN HORSES AND PONIES SIX MONTHS OF AGE AND OLDER

NADA 141-087, Approved by FDA

INDICATIONS

QUEST (moxidectin) 2% Equine Oral Gel when administered at the recommended dose level of 0.4 mg moxidectin/kg (2.2 lb) body weight is effective in the treatment and control of the following stages of gastrointestinal parasites in horses and ponies:

Large Strongyles:

- Strongylus vulgaris – (adults and L4/L5 arterial stages)
- Strongylus edentatus – (adults and tissue stages)
- Triodontophorus brevicauda – (adults)
- Triodontophorus serratus – (adults)

Small Strongyles (adults):

- Cyathostomum spp., including
  - Cyathostomum catinatum
  - Cyathostomum pateratum
- Cylicostephanus spp., including
  - Cylicostephanus calicatus
  - Cylicostephanus goldi
  - Cylicostephanus longibursatus
  - Cylicostephanus minutus
- Cylicocyclus spp., including
  - Cylicocyclus insigne
  - Cylicocyclus leptostomum
  - Cylicocyclus nassatus
  - Cylicocyclus radiatus
- Coronocyclus spp., including
  - Coronocyclus coronatus
  - Coronocyclus labiatus
  - Coronocyclus labratus
  - Gyalocephalus capitatus
  - Petrovinema poculatus

Small Strongyles:

Undifferentiated lumenal larvae

Encysted cyathostomes

Late L3 and L4 mucosal cyathostome larvae

Ascarids

Parascaris equorum – (adults and L4 larval stages)

Pinworms

Oxyuris equi – (adults and L4 larval stages)

Hairworms

Trichostrongylus axei – (adults)

Large-mouth stomach worms

Habronema muscae – (adults)

Horse stomach bots

Gasterophilus intestinalis – (2nd and 3rd instars)
Gasterophilus nasalis – (3rd instars)

One administration of the recommended dose rate of QUEST (moxidectin) 2% Equine Oral Gel also suppresses strongyle egg production through 84 days. QUEST is indicated for use in horses and ponies, including breeding mares and stallions, and foals six months of age and older.

STRATEGIC PROTECTION PROGRAMS

Consult your veterinarian for assistance in the diagnosis, treatment, and control of parasitism. For best control of parasites, all horses and ponies should be included in a strategic treatment program, with particular attention given to high performance animals, brood mares, stallions and foals. In foals, initial treatment is recommended at 6 months of age, after which they should be included in a recurrent treatment program. Because QUEST provides effective control of the mucosal stages of small strongyles (encysted cyathostomes), it is useful in reducing the frequency of treatment required for successful strategic equine parasite control. A veterinarian can assist in preparing the best program for your needs.

QUEST 2% Equine Oral Gel when used at the recommended dose rate suppresses strongyle egg production through 84 days following a single oral administration. This residual strongyle control reduces pasture contamination and provides a period of protection from reinfection for horses and ponies maintained on the same pasture.

MODE OF ACTION

QUEST 2% Equine Oral Gel acts by interfering with chloride channel-mediated neurotransmission in the parasite. This results in paralysis and elimination of the parasite. Moxidectin is safe for use in horses and ponies because it does not have the same injurious effect on the mammalian nervous system.

ADMINISTRATION AND DOSAGE

QUEST (moxidectin) 2% Equine Oral Gel is specially formulated as a palatable gel which is easily
administered to horses and ponies. QUEST Gel is packaged in ready-to-use SURE-DIAL® syringes. The
syringe is calibrated in 50-pound increments, up to 1500 pounds. This enables the administration of
the recommended dose level of 0.4 mg moxidectin/kg body weight by choosing a setting consistent
with the animal’s weight.

HOW TO SET THE DOSE

Since the dose is based on the weight of the animal, you need to use a scale or weight tape to fi nd
each animal’s weight before treating with QUEST Gel. Once the weight is known, set the dose for
each horse or pony as follows.
1. Hold the syringe with the capped end pointing to the left and so that you can see the weight
measurements and tick marks (small black lines). Each tick mark relates to 50 lb of body weight.
2. Turn the white dial ring until the left side of the ring lines up with the weight of the animal

HOW TO GIVE QUEST GEL TO A HORSE OR PONY

1. Make sure there is no feed in the animal’s mouth.
2. Remove the cap from the end of the syringe. Save the cap for reuse.
3. Place the tip of the syringe inside the animal’s mouth at the space between the teeth.
4. Gently push the plunger until it stops, depositing the gel on the back of the tongue.
5. Remove the syringe from the animal’s mouth and raise the animal’s head slightly to make sure it
swallows the gel.
6. Replace the syringe cap.

TREATING A SECOND HORSE OR PONY WITH THE SAME SYRINGE

If the first animal you treat weighs less than 1500 lb, there will be gel left in the syringe. You can use

this gel to treat other horses or ponies. To set the next dose, add the weight of the animal you want

to treat to the dose setting already on the syringe. For example, if the syringe was first used to treat a

250 lb animal, the white dial ring is set on 250 lb. To treat a 500 lb animal next, move the white dial ring

to the 750 lb marking (250+500=750). You need more than one syringe to treat horses weighing more

than 1500 lb.

ANIMAL SAFETY

QUEST (moxidectin) 2% Equine Oral Gel can be safely administered at the recommended dose of 0.4 mg
moxidectin/kg body weight to horses and ponies of all breeds at least 6 months of age or older. Transient
depression, ataxia and recumbency may be seen when very young or debilitated animals are treated.
In these instances, supportive care may be advisable.
Reproductive safety studies demonstrate a wide margin of safety when the product is used in the
treatment of estrual and pregnant mares and breeding stallions.
To report adverse drug reactions or to obtain a copy of the Safety Data Sheet (SDS) call 1-888-963-8471.

ENVIRONMENTAL SAFETY

Care should be taken to avoid the release of significant volumes of moxidectin into either ground or free-running water since moxidectin may be injurious to aquatic life. SURE-DIAL® syringes and their contents should be disposed of in an approved landfill or by incineration.

PRECAUTIONS

QUEST 2% Equine Oral Gel has been formulated specifically for use in horses and ponies only. This product should not be used in other animal species as severe adverse reactions, including fatalities in dogs, may result.

WARNINGS

Extreme caution should be used when administering the product to foals, young and miniature horses, as overdosage may result in serious adverse reactions. Do not use in sick, debilitated, or underweight animals. Do not use in horses intended for human consumption.

HUMAN WARNINGS

Not for use in humans. Keep this and all drugs out of the reach of children. Do not ingest. If swallowed, induce vomiting. Wash hands and contaminated skin with soap and water. If accidental contact with eyes occurs, flush repeatedly with water. If irritation or any other symptom attributable to exposure to this product persists, consult your physician.

HOW SUPPLIED

QUEST 2% Equine Oral Gel is available in one syringe applicator size.
Each SURE-DIAL® syringe contains 0.5 oz (14.4 g) of QUEST 2% Equine Oral Gel which is suffi cient to
treat a single horse weighing up to 1500 lb, or two or more lighter animals with a combined body
weight of up to 1500 lb.

0.5 oz (14.4 g) syringe - 20 mg moxidectin per mL

Store at or below 77°F (25°C). Avoid freezing. If frozen, thaw completely before use.
Store partially-used syringes with the cap tightly secured.

Distributed by:

Zoetis Inc.

Kalamazoo, MI 49007

Product of Italy

Made in Spain

Revised: January 2018

40016422

PRINCIPAL DISPLAY PANEL - 11.3 g Syringe Carton

Net Contents: One syringe
containing 0.4 oz (11.3 g)
moxidectin gel

QUEST® GEL
(moxidectin)

FOR ORAL USE IN HORSES AND PONIES

SIX MONTHS OF AGE AND OLDER

LARGER DOSE TREATS

UP TO 1500 LBS

HORSE DEWORMER
& BOTICIDE

zoetis